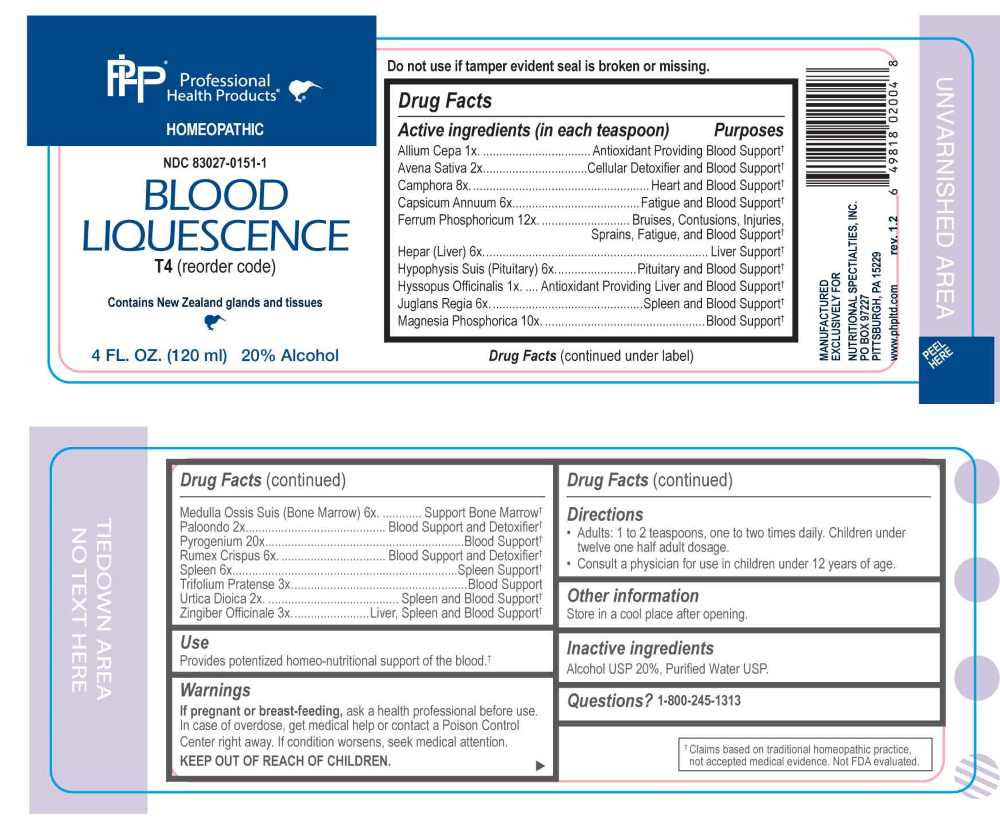 DRUG LABEL: Blood Liquescence
NDC: 83027-0151 | Form: LIQUID
Manufacturer: Nutritional Specialties, Inc.
Category: homeopathic | Type: HUMAN OTC DRUG LABEL
Date: 20250922

ACTIVE INGREDIENTS: ONION 1 [hp_X]/1 mL; HYSSOPUS OFFICINALIS FLOWERING TOP 1 [hp_X]/1 mL; AVENA SATIVA FLOWERING TOP 2 [hp_X]/1 mL; LARREA TRIDENTATA LEAF 2 [hp_X]/1 mL; URTICA DIOICA WHOLE 2 [hp_X]/1 mL; TRIFOLIUM PRATENSE FLOWER 3 [hp_X]/1 mL; GINGER 3 [hp_X]/1 mL; CAPSICUM 6 [hp_X]/1 mL; HEPARIN, BOVINE 6 [hp_X]/1 mL; SUS SCROFA PITUITARY GLAND 6 [hp_X]/1 mL; JUGLANS REGIA LEAF 6 [hp_X]/1 mL; SUS SCROFA BONE MARROW 9 [hp_X]/1 mL; RUMEX CRISPUS ROOT 6 [hp_X]/1 mL; BOS TAURUS SPLEEN 6 [hp_X]/1 mL; CAMPHOR (NATURAL) 8 [hp_X]/1 mL; MAGNESIUM PHOSPHATE, DIBASIC TRIHYDRATE 10 [hp_X]/1 mL; FERROSOFERRIC PHOSPHATE 12 [hp_X]/1 mL; RANCID BEEF 20 [hp_X]/1 mL
INACTIVE INGREDIENTS: WATER; ALCOHOL

DRUG FACTS:

ACTIVE INGREDIENTS:

Allium Cepa 1X, Avena Sativa 2X, Camphora 8X, Capsicum Annuum 6X, Ferrum Phosphoricum 12X, Hepar 6X, Hypophysis Suis 6X, Hyssopus Officinalis 1X, Juglans Regia 6X, Magnesia Phosphorica 10X, Medulla Ossis Suis 6X, Paloondo 2X, Pyrogenium 20X, Remex Crispus 6X, Spleen 6X, Trifolium Pratense 3X, Urtica Dioica 2X, Zingiber Officinale 3X.

PURPOSE:

Allium Cepa – Antioxidant Providing Blood Support,† Avena Sativa – Cellular Detoxifier and Blood Support,† Camphora – Heart and Blood Support,† Capsicum Annuum – Fatigue and Blood Support,† Ferrum Phosphoricum – Bruises, Contusions, Injuries, Sprains, Fatigue, and Blood Support,† Hepar - Liver Support,† Hypophysis Suis – Pituitary and Blood Support,† Hyssopus Officinalis – Antioxidant Providing Liver and Blood Support,† Juglans Regia – Spleen and Blood Support,† Magnesia Phosphorica – Blood Support,† Medulla Ossis Suis – Support Bone Marrow,† Paloondo – Blood Support and Detoxifier, Pyrogenium – Blood Support, Remex Crispus - Blood Support and Detoxifier, Spleen – Spleen Support, Trifolium Pratense – Blood Support,† Urtica Dioica – Spleen and Blood Support,† Zingiber Officinale – Liver, Spleen and Blood Support†

†Claims based on traditional homeopathic practice, not accepted medical evidence. Not FDA evaluated.

USES:

Provides potentized homeo-nutritional support of the blood.†

†Claims based on traditional homeopathic practice, not accepted medical evidence. Not FDA evaluated.

WARNINGS:

If pregnant or breast-feeding, ask a health professional before use.

In case of overdose, get medical help or contact a Poison Control Center right away.

If condition worsens, seek medical attention.

KEEP OUT OF REACH OF CHILDREN

Do not use if tamper evident seal is broken or missing.

Store in a cool place after opening

KEEP OUT OF REACH OF CHILDREN:

In case of overdose, get medical help or contact a Poison Control Center right away.

DIRECTIONS:

• Adults: 1 to 2 teaspoons, one to two times daily. Children under twelve one half adult dosage.

• Consult a physician for use in children under 12 years of age.

INACTIVE INGREDIENTS:

Alcohol USP 20%, Purified Water USP.

QUESTIONS:

MANUFACTURED EXCLUSIVELY FOR

NUTRITIONAL SPECIALTIES, INC.

PO BOX 97227

PITTSBURGH, PA 15229

www.phpitd.com

PACKAGE LABEL DISPLAY:

Professional Health Products

HOMEOPATHIC

NDC 83027-0151-1

BLOOD LIQUESCENCE

4 FL. OZ. (120 ml)